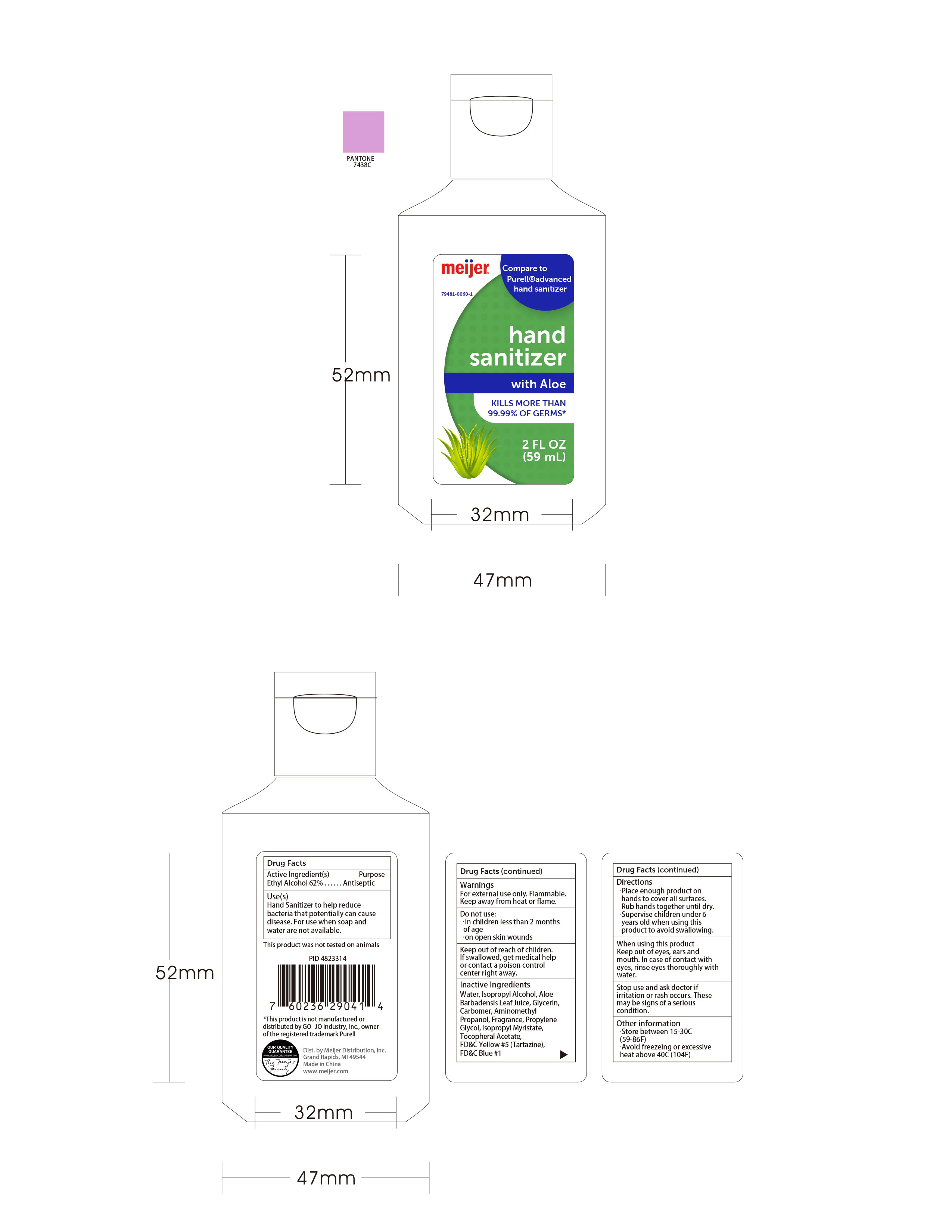 DRUG LABEL: meijer hand sanitizer 59ml
NDC: 79481-0060 | Form: GEL
Manufacturer: Meijer, Inc.
Category: otc | Type: HUMAN OTC DRUG LABEL
Date: 20201204

ACTIVE INGREDIENTS: ALCOHOL 62 mL/100 mL
INACTIVE INGREDIENTS: ISOPROPYL MYRISTATE 0.001 mL/100 mL; ALOE 0.1 mL/100 mL; FD&C BLUE NO. 1 0.000024 mL/100 mL; WATER 37.197916 mL/100 mL; ALOE VERA LEAF 0.05 mL/100 mL; CARBOMER 940 0.26 mL/100 mL; AMINOMETHYLPROPANOL 0.09 mL/100 mL; GLYCERIN 0.1 mL/100 mL; .ALPHA.-TOCOPHEROL ACETATE 0.001 mL/100 mL; FD&C YELLOW NO. 5 0.00006 mL/100 mL; ISOPROPYL ALCOHOL 0.1 mL/100 mL; PROPYLENE GLYCOL 0.1 mL/100 mL

meijer hand sanitizer 59ml

Active Ingredient

Active Ingredient Purpose

Ethyl Alcohol 62% Antiseptic

Use(s)

Hand sanitizer to help reduce bacteria that potentially can cause disease.For use when soap and water are not available.

DOSAGE AND ADMINISTRATION

Recommended for repeated use.

use anywhere without water.

Warnings

For external use only.Flammable.Keep away from heat or flame.

WARNINGS AND PRECAUTIONS

For external use only.

Flammable, keep away from heat and flame.

STOP USE

Discontinue if skin becomes irritated and ask a doctor .

Keep out of reach of children. In case of accidental ingestion, seek professional assistance or contact a poson control center immediately.

Inactive ingredients

Aqua,Isopropyl Alcohol,Aloe Barbadensis Leaf Water,Glycerin,Carbomer,Aminomethyl Propanol,Fragrance,Propylene Glycol，Isopropyl Myristate,Tocopheryl Acetate,FD&C Yellow #5(Tartazine),FD&C Blue #1.

Directions

Place enough product on hands to cover all surfaces.Rub hands together until dry.Supervise children under 6 years old when using this product to avoid swallowing.

When using this product

keep out of eyes. In case of contact with eyes, flush thoroughly with water.

Do not inhale or ingest.

Avoid contact with broken skin.

Other information

Do not store above 105F.

May discolor some fabrics.

Harmful to wood finishes and plastics.

When using this product

keep out of eyes,ears and mouth.In case of contact with eyes,rinse eyes thoroughly with water.

Do not use

in children less than 2 months of age.

on open skin wounds.

Keep out of reach of children

If swallowed,get medical help or contact a poison control center right away.

Stop use and ask doctor if

irritation or rash occurs,These may be signs of serious conditon.

Other information

Store between 15-30C(59-86F）

Avoid freezing or excessive heat above 40C(104F）